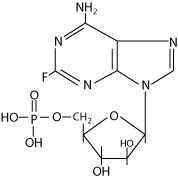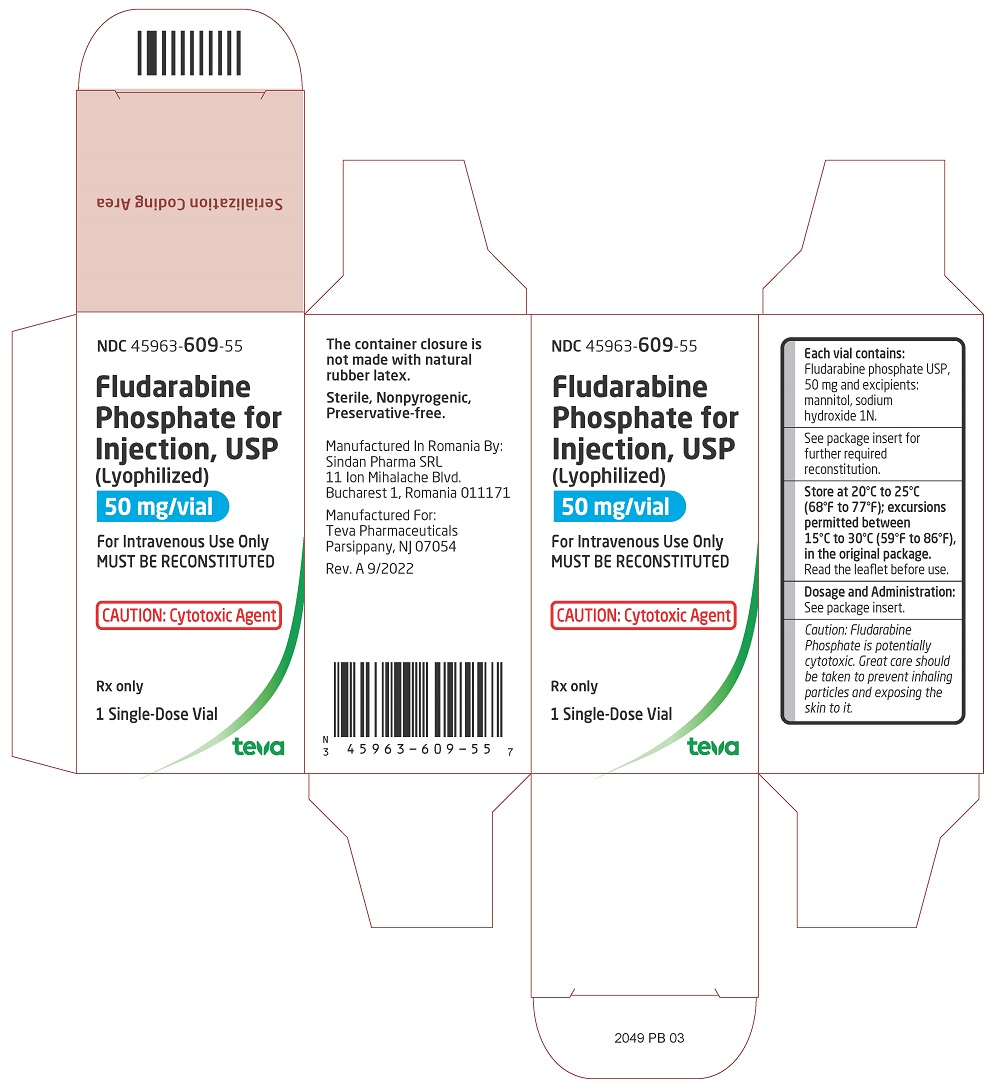 DRUG LABEL: Fludarabine phosphate
NDC: 45963-609 | Form: INJECTION, POWDER, LYOPHILIZED, FOR SOLUTION
Manufacturer: Actavis Pharma, Inc.
Category: prescription | Type: HUMAN PRESCRIPTION DRUG LABEL
Date: 20220930

ACTIVE INGREDIENTS: FLUDARABINE PHOSPHATE 50 mg/2 mL
INACTIVE INGREDIENTS: MANNITOL; SODIUM HYDROXIDE

Fludarabine Phosphate for Injection, USP

For Intravenous Use Only

Rx only

WARNING:

Fludarabine Phosphate for Injection should be administered under the supervision of a qualified physician experienced in the use of antineoplastic therapy. Fludarabine Phosphate for Injection can severely suppress bone marrow function. When used at high doses in dose-ranging studies in patients with acute leukemia, Fludarabine Phosphate for Injection was associated with severe neurologic effects, including blindness, coma, and death. This severe central nervous system toxicity occurred in 36% of patients treated with doses approximately four times greater (96 mg/m^2/day for 5 to 7 days) than the recommended dose. Similar severe central nervous system toxicity, including coma, seizures, agitation and confusion, has been reported in patients treated at doses in the range of the dose recommended for chronic lymphocytic leukemia.

Instances of life-threatening and sometimes fatal autoimmune phenomena such as hemolytic anemia, autoimmune thrombocytopenia/thrombocytopenic purpura (ITP), Evans syndrome, and acquired hemophilia have been reported to occur after one or more cycles of treatment with Fludarabine Phosphate for Injection. Patients undergoing treatment with Fludarabine Phosphate for Injection should be evaluated and closely monitored for hemolysis.

In a clinical investigation using Fludarabine Phosphate for Injection in combination with pentostatin (deoxycoformycin) for the treatment of refractory chronic lymphocytic leukemia (CLL), there was an unacceptably high incidence of fatal pulmonary toxicity. Therefore, the use of Fludarabine Phosphate for Injection in combination with pentostatin is not recommended.

DESCRIPTION

Fludarabine Phosphate for Injection, USP contains fludarabine phosphate USP, a fluorinated nucleotide analog of the antiviral agent vidarabine, 9-β-D-arabinofuranosyladenine (ara-A) that is relatively resistant to deamination by adenosine deaminase. Each vial of sterile lyophilized solid cake contains 50 mg of the active ingredient fludarabine phosphate, 50 mg of mannitol, and sodium hydroxide to adjust pH to 7.7. The pH range for the final product is 7.2 to 8.2. Reconstitution with 2 mL of Sterile Water for Injection, USP, results in a solution containing 25 mg/mL of fludarabine phosphate intended for intravenous administration.

The chemical name for fludarabine phosphate is 9H-Purin-6-amine, 2-fluoro-9-(5-0-phosphono-β-D-arabino-furanosyl) (2-fluoro-ara-AMP). The molecular formula of fludarabine phosphate is C10H13FN5O7P (MW 365.2) and the structure is:

CLINICAL PHARMACOLOGY

Fludarabine phosphate is rapidly dephosphorylated to 2-fluoro-ara-A and then phosphorylated intracellularly by deoxycytidine kinase to the active triphosphate, 2-fluoro-ara-ATP. This metabolite appears to act by inhibiting DNA polymerase alpha, ribonucleotide reductase and DNA primase, thus inhibiting DNA synthesis. The mechanism of action of this antimetabolite is not completely characterized and may be multi-faceted.

Phase I studies in humans have demonstrated that fludarabine phosphate is rapidly converted to the active metabolite, 2-fluoro-ara-A, within minutes after intravenous infusion. Consequently, clinical pharmacology studies have focused on 2-fluoro-ara-A pharmacokinetics. After the five daily doses of
25 mg 2-fluoro-ara-AMP/m^2 to cancer patients infused over 30 minutes, 2-fluoro-ara-A concentrations show a moderate accumulation. During a 5-day treatment schedule, 2-fluoro-ara-A plasma trough levels increased by a factor of about 2. The terminal half-life of 2-fluoro-ara-A was estimated as approximately 20 hours. In vitro, plasma protein binding of fludarabine ranged between 19% and 29%.

A correlation was noted between the degree of absolute granulocyte count nadir and increased area under the concentration x time curve (AUC).

Special Populations

Pediatric Patients

Limited pharmacokinetic data for Fludarabine Phosphate for Injection are available from a published study of children (ages 1 to 21 years) with refractory acute leukemias or solid tumors (Children's Cancer Group Study 097^1). When Fludarabine Phosphate for Injection was administered as a loading dose over 10 minutes immediately followed by a 5-day continuous infusion, steady-state conditions were reached early.

Patients with Renal Impairment

The total body clearance of the principal metabolite 2-fluoro-ara-A correlated with the creatinine clearance, indicating the importance of the renal excretion pathway for the elimination of the drug. Renal clearance represents approximately 40% of the total body clearance. Patients with creatinine clearance 30 to 79 mL/min should have their Fludarabine Phosphate for Injection dose reduced and be monitored closely for excessive toxicity. Due to insufficient data, Fludarabine Phosphate for Injection should not be administered to patients with creatinine clearance less than 30 mL/min (see DOSAGE AND ADMINISTRATION section).

CLINICAL STUDIES

Two single-arm, open-label studies of Fludarabine Phosphate for Injection have been conducted in adult patients with CLL refractory to at least one prior standard alkylating-agent containing regimen. In a study conducted by M.D. Anderson Cancer Center (MDAH), 48 patients were treated with a dose of 22 to 40 mg/m^2 daily for 5 days every 28 days. Another study conducted by the Southwest Oncology Group (SWOG) involved 31 patients treated with a dose of 15 to 25 mg/m^2 daily for 5 days every 28 days. The overall objective response rates were 48% and 32% in the MDAH and SWOG studies, respectively. The complete response rate in both studies was 13%; the partial response rate was 35% in the MDAH study and 19% in the SWOG study. These response rates were obtained using standardized response criteria developed by the National Cancer Institute CLL Working Group and were achieved in heavily pretreated patients. The ability of Fludarabine Phosphate for Injection to induce a significant rate of response in refractory patients suggests minimal cross-resistance with commonly used anti-CLL agents.

The median time to response in the MDAH and SWOG studies was 7 weeks (range of 1 to 68 weeks) and 21 weeks (range of 1 to 53 weeks), respectively. The median duration of disease control was 91 weeks (MDAH) and 65 weeks (SWOG). The median survival of all refractory CLL patients treated with Fludarabine Phosphate for Injection was 43 weeks and 52 weeks in the MDAH and SWOG studies, respectively.

Rai stage improved to Stage II or better in 7 of 12 MDAH responders (58%) and in 5 of 7 SWOG responders (71%) who were Stage III or IV at baseline. In the combined studies, mean hemoglobin concentration improved from 9 g/dL at baseline to 11.8 g/dL at the time of response in a subgroup of anemic patients. Similarly, average platelet count improved from 63,500/mm^3 to 103,300/mm^3 at the time of response in a subgroup of patients who were thrombocytopenic at baseline.

INDICATIONS AND USAGE

Fludarabine Phosphate for Injection is indicated for the treatment of adult patients with B-cell chronic lymphocytic leukemia (CLL) who have not responded to or whose disease has progressed during treatment with at least one standard alkylating-agent containing regimen. The safety and effectiveness of Fludarabine Phosphate for Injection in previously untreated or non-refractory patients with CLL have not been established.

CONTRAINDICATIONS

Fludarabine Phosphate for Injection is contraindicated in those patients who are hypersensitive to this drug or its components.

WARNINGS

(See BOXED WARNINGS)

Dose Dependent Neurologic Toxicities

There are clear dose-dependent toxic effects seen with Fludarabine Phosphate for Injection. Dose levels approximately 4 times greater (96 mg/m^2/day for 5 to 7 days) than that recommended for CLL (25 mg/m^2/day for 5 days) were associated with a syndrome characterized by delayed blindness, coma and death. Symptoms appeared from 21 to 60 days following the last dose. Thirteen of 36 patients (36%) who received Fludarabine Phosphate for Injection at high doses (96 mg/m^2/day for 5 to 7 days) developed this severe neurotoxicity. Similar severe central nervous system toxicity, including coma, seizures, agitation and confusion, has been reported in patients treated at doses in the range of the dose recommended for chronic lymphocytic leukemia.

In post-marketing experience neurotoxicity has been reported to occur either earlier or later than in clinical trials (range 7 to 225 days).

The effect of chronic administration of Fludarabine Phosphate for Injection on the central nervous system is unknown; however, patients have received the recommended dose for up to 15 courses of therapy.

Bone Marrow Suppression

Severe bone marrow suppression, notably anemia, thrombocytopenia and neutropenia, has been reported in patients treated with Fludarabine Phosphate for Injection. In a Phase I study in adult solid tumor patients, the median time to nadir counts was 13 days (range, 3 to 25 days) for granulocytes and 16 days (range, 2 to 32) for platelets. Most patients had hematologic impairment at baseline either as a result of disease or as a result of prior myelosuppressive therapy. Cumulative myelosuppression may be seen. While chemotherapy-induced myelosuppression is often reversible, administration of Fludarabine Phosphate for Injection requires careful hematologic monitoring.

Several instances of trilineage bone marrow hypoplasia or aplasia resulting in pancytopenia, sometimes resulting in death, have been reported in adult patients. The duration of clinically significant cytopenia in the reported cases has ranged from approximately 2 months to approximately 1 year. These episodes have occurred both in previously treated or untreated patients.

Autoimmune Reactions

Instances of life-threatening and sometimes fatal autoimmune phenomena such as hemolytic anemia, autoimmune thrombocytopenia/thrombocytopenic purpura (ITP), Evans syndrome, and acquired hemophilia have been reported to occur after one or more cycles of treatment with Fludarabine Phosphate for Injection in patients with or without a previous history of autoimmune hemolytic anemia or a positive Coombs' test and who may or may not be in remission from their disease. Steroids may or may not be effective in controlling these hemolytic episodes. The majority of patients rechallenged with Fludarabine Phosphate for Injection developed a recurrence in the hemolytic process. The mechanism(s) which predispose patients to the development of this complication has not been identified. Patients undergoing treatment with Fludarabine Phosphate for Injection should be evaluated and closely monitored for hemolysis. Discontinuation of therapy with Fludarabine Phosphate for Injection is recommended in case of hemolysis.

Transfusion-associated graft-versus-host disease has been observed after transfusion of non-irradiated blood in Fludarabine Phosphate for Injection treated patients. Fatal outcome as a consequence of this disease has been reported. Therefore, to minimize the risk of transfusion-associated graft-versus-host disease, patients who require blood transfusion and who are undergoing, or who have received, treatment with Fludarabine Phosphate for Injection should receive irradiated blood only.

Pulmonary Toxicity

In a clinical investigation using Fludarabine Phosphate for Injection in combination with pentostatin (deoxycoformycin) for the treatment of refractory chronic lymphocytic leukemia (CLL) in adults, there was an unacceptably high incidence of fatal pulmonary toxicity. Therefore, the use of Fludarabine Phosphate for Injection in combination with pentostatin is not recommended.

Pregnancy Category D

Based on its mechanism of action, fludarabine phosphate can cause fetal harm when administered to a pregnant woman. There are no adequate and well-controlled studies of Fludarabine Phosphate for Injection in pregnant women. Fludarabine administered to rats and rabbits during organogenesis caused an increase in resorptions, skeletal and visceral malformations and decreased fetal body weights. If Fludarabine Phosphate for Injection is used during pregnancy, or if the patient becomes pregnant while taking this drug, the patient should be apprised of the potential hazard to the fetus. Women of childbearing potential should be advised to avoid becoming pregnant.

Male Fertility and Reproductive Outcomes

Males with female sexual partners of childbearing potential should use contraception during and after cessation of Fludarabine Phosphate for Injection therapy. Fludarabine may damage testicular tissue and spermatozoa. Possible sperm DNA damage raises concerns about loss of fertility and genetic abnormalities in fetuses. The duration of this effect is uncertain. (See PRECAUTIONS, Impairment of Fertility)

PRECAUTIONS

General

Fludarabine Phosphate for Injection is a potent antineoplastic agent with potentially significant toxic side effects. Patients undergoing therapy should be closely observed for signs of hematologic and nonhematologic toxicity. Periodic assessment of peripheral blood counts is recommended to detect the development of anemia, neutropenia and thrombocytopenia.

In patients with impaired state of health, Fludarabine Phosphate for Injection should be given with caution and after careful risk/benefit consideration. This applies especially for patients with severe impairment of bone marrow function (thrombocytopenia, anemia, and/or granulocytopenia), immunodeficiency or with a history of opportunistic infection. Prophylactic treatment should be considered in patients at increased risk of developing opportunistic infections.

Fludarabine Phosphate for Injection may reduce the ability to drive or use machines, since fatigue, weakness, visual disturbances, confusion, agitation and seizures have been observed.

Tumor Cell Lysis

Tumor lysis syndrome has been associated with Fludarabine Phosphate for Injection treatment. This syndrome has been reported in CLL patients with large tumor burden. Since Fludarabine Phosphate for Injection can induce a response as early as the first week of treatment, precautions should be taken in those patients at risk of developing this complication.

Renal Impairment

Fludarabine Phosphate for Injection must be administered cautiously in patients with renal impairment. The total body clearance of 2-fluoro-ara-A has been shown to be directly correlated with creatinine clearance. Patients with creatinine clearance 30 to 79 mL/min should have their Fludarabine Phosphate for Injection dose reduced and be monitored closely for excessive toxicity. Fludarabine Phosphate for Injection should not be administered to patients with creatinine clearance less than 30 mL/min. (See DOSAGE AND ADMINISTRATION section).

In patients aged 65 years or older, creatinine clearance should be measured before start of treatment.

Laboratory Tests

During treatment, the patient's hematologic profile (particularly neutrophils and platelets) should be monitored regularly to determine the degree of hematopoietic suppression.

Drug Interactions

The use of Fludarabine Phosphate for Injection in combination with pentostatin is not recommended due to the risk of fatal pulmonary toxicity (see WARNINGS section).

Carcinogenesis

No animal carcinogenicity studies with Fludarabine Phosphate for Injection have been conducted.

Mutagenesis

Fludarabine phosphate was not mutagenic to bacteria (Ames test) or mammalian cells (HGRPT assay in Chinese hamster ovary cells) either in the presence or absence of metabolic activation. Fludarabine phosphate was clastogenic in vitro to Chinese hamster ovary cells (chromosome aberrations in the presence of metabolic activation) and induced sister chromatid exchanges both with and without metabolic activation. In addition, fludarabine phosphate was clastogenic in vivo (mouse micronucleus assay) but was not mutagenic to germ cells (dominant lethal test in male mice).

Impairment of Fertility

Studies in mice, rats and dogs have demonstrated dose-related adverse effects on the male reproductive system. Observations consisted of a decrease in mean testicular weights in mice and rats with a trend toward decreased testicular weights in dogs and degeneration and necrosis of spermatogenic epithelium of the testes in mice, rats and dogs. The possible adverse effects on fertility in humans have not been adequately evaluated.

Pregnancy

(See WARNINGS section).

Based on its mechanism of action, fludarabine phosphate can cause fetal harm when administered to a pregnant woman. There are not adequate and well-controlled studies of fludarabine phosphate in pregnant women. Fludarabine phosphate was embryolethal and teratogenic in rats and rabbits. If Fludarabine Phosphate for Injection is used during pregnancy, or if the patient becomes pregnant while taking this drug, the patient should be apprised of the potential hazard to the fetus. Women of childbearing potential should be advised to avoid becoming pregnant.

In rats, repeated intravenous doses of fludarabine phosphate at 2.4 times and 7.2 times the recommended human IV dose (25 mg/m^2) administered during organogenesis caused an increase in resorptions, skeletal and visceral malformations (cleft palate, exencephaly, and fetal vertebrae deformities) and decreased fetal body weights. Maternal toxicity was not apparent at 2.4 times the human IV dose, and was limited to slight body weight decreases at 7.2 times the human IV dose. In rabbits, repeated intravenous doses of fludarabine phosphate at 3.8 times the human IV dose administered during organogenesis increased embryo and fetal lethality as indicated by increased resorptions and a decrease in live fetuses. A significant increase in malformations including cleft palate, hydrocephaly, adactyly, brachydactyly, fusions of the digits, diaphragmatic hernia, heart/great vessel defects, and vertebrae/rib anomalies were seen in all dose levels (≥0.5 times the human IV dose).

Nursing Mothers

It is not known whether fludarabine phosphate is excreted in human milk. Because many drugs are excreted in human milk and because of the potential for serious adverse reactions including tumorgenicity in nursing infants, a decision should be made to discontinue nursing or discontinue the drug, taking into account the importance of the drug to the mother.

Pediatric Use

Data submitted to the FDA was insufficient to establish efficacy in any childhood malignancy. Fludarabine Phosphate for Injection was evaluated in 62 pediatric patients (median age 10, range 1 to 21) with refractory acute leukemia (45 patients) or solid tumors (17 patients). The Fludarabine Phosphate for Injection regimen tested for pediatric acute lymphocytic leukemia (ALL) patients was a loading bolus of 10.5 mg/m^2/day followed by a continuous infusion of 30.5 mg/m^2/day for 5 days. In 12 pediatric patients with solid tumors, dose-limiting myelosuppression was observed with a loading dose of 8 mg/m^2/day followed by a continuous infusion of 23.5 mg/m^2/day for 5 days. The maximum tolerated dose was a loading dose of 7 mg/m^2/day followed by a continuous infusion of 20 mg/m^2/day for 5 days. Treatment toxicity included bone marrow suppression. Platelet counts appeared to be more sensitive to the effects of Fludarabine Phosphate for Injection than hemoglobin and white blood cell counts. Other adverse events included fever, chills, asthenia, rash, nausea, vomiting, diarrhea, and infection. There were no reported occurrences of peripheral neuropathy or pulmonary hypersensitivity reaction.

Vaccination

During and after treatment with Fludarabine Phosphate for Injection, vaccination with live vaccines should be avoided.

Disease Progression

Richter’s syndrome has been reported in CLL patients.

ADVERSE REACTIONS

Very common adverse events include myelosuppression (neutropenia, thrombocytopenia and anemia), fever and chills, fatigue, weakness, infection, pneumonia, cough, nausea, vomiting, and diarrhea. Other commonly reported events include malaise, mucositis and anorexia. Serious opportunistic infections (such as latent viral reactivation, herpes zoster virus, Epstein-Barr virus, and progressive multifocal leukoencephalopathy) have occurred in CLL patients treated with Fludarabine Phosphate for Injection. Adverse events and those reactions which are more clearly related to the drug are arranged below according to body system.

Hematopoietic Systems

Hematologic events (neutropenia, thrombocytopenia, and/or anemia) were reported in the majority of CLL patients treated with Fludarabine Phosphate for Injection. During Fludarabine Phosphate for Injection treatment of 133 patients with CLL, the absolute neutrophil count decreased to less than 500/mm^3 in 59% of patients, hemoglobin decreased from pretreatment values by at least 2 grams percent in 60%, and platelet count decreased from pretreatment values by at least 50% in 55%. Myelosuppression may be severe, cumulative, and may affect multiple cell lines. Bone marrow fibrosis occurred in one CLL patient treated with Fludarabine Phosphate for Injection.

Several instances of trilineage bone marrow hypoplasia or aplasia resulting in pancytopenia, sometimes resulting in death, have been reported in post marketing surveillance. The duration of clinically significant cytopenia in the reported cases has ranged from approximately 2 months to approximately 1 year. These episodes have occurred both in previously treated or untreated patients.

Life-threatening and sometimes fatal autoimmune phenomena such as hemolytic anemia, autoimmune thrombocytopenia/thrombocytopenic purpura (ITP), Evans syndrome, and acquired hemophilia have been reported to occur in patients receiving Fludarabine Phosphate for Injection (see WARNINGS section). The majority of patients rechallenged with Fludarabine Phosphate for Injection developed a recurrence in the hemolytic process.

In postmarketing experience, cases of myelodysplastic syndrome and acute myeloid leukemia, mainly associated with prior, concomitant or subsequent treatment with alkylating agents, topoisomerase inhibitors, or irradiation have been reported.

Infections

Serious and sometimes fatal infections, including opportunistic infections and reactivations of latent viral infections such as VZV (herpes zoster), Epstein-Barr virus and JC virus (progressive multifocal leukoencephalopathy) have been reported in patients treated with Fludarabine Phosphate for Injection.

Rare cases of Epstein Barr virus (EBV) associated lymphoproliferative disorders have been reported in patients treated with Fludarabine Phosphate for Injection.

In postmarketing experience, cases of progressive multifocal leukoencephalopathy have been reported. Most cases had a fatal outcome. Many of these cases were confounded by prior and/or concurrent chemotherapy. The time to onset has ranged from a few weeks to approximately one year after initiating treatment.

Of the 133 adult CLL patients in the two trials, there were 29 fatalities during study, approximately 50% of which were due to infection.

Metabolic

Tumor lysis syndrome has been reported in CLL patients treated with Fludarabine Phosphate for Injection. This complication may include hyperuricemia, hyperphosphatemia, hypocalcemia, metabolic acidosis, hyperkalemia, hematuria, urate crystalluria, and renal failure. The onset of this syndrome may be heralded by flank pain and hematuria.

Nervous System (see WARNINGS section)

Objective weakness, agitation, confusion, seizures, visual disturbances, optic neuritis, optic neuropathy, blindness and coma have occurred in CLL patients treated with Fludarabine Phosphate for Injection at the recommended dose. Peripheral neuropathy has been observed in patients treated with Fludarabine Phosphate for Injection and one case of wrist-drop was reported. There have been additional reports of cerebral hemorrhage though the frequency is not known.

Pulmonary System

Pneumonia, a frequent manifestation of infection in CLL patients, occurred in 16% and 22% of those treated with Fludarabine Phosphate for Injection in the MDAH and SWOG studies, respectively. Pulmonary hypersensitivity reactions to Fludarabine Phosphate for Injection characterized by dyspnea, cough and interstitial pulmonary infiltrate have been observed.

In post-marketing experience, cases of severe pulmonary toxicity have been observed with Fludarabine Phosphate for Injection use which resulted in ARDS, respiratory distress, pulmonary hemorrhage, pulmonary fibrosis, pneumonitis and respiratory failure. After an infectious origin has been excluded, some patients experienced symptom improvement with corticosteroids.

Gastrointestinal System

Gastrointestinal disturbances such as nausea and vomiting, anorexia, diarrhea, stomatitis and gastrointestinal bleeding and hemorrhage have been reported in patients treated with Fludarabine Phosphate for Injection. Elevations of pancreatic enzyme levels have also been reported.

Cardiovascular

Edema has been frequently reported. One patient developed a pericardial effusion possibly related to treatment with Fludarabine Phosphate for Injection. There have been additional reports of heart failure and arrhythmia though the frequency is rare. No other severe cardiovascular events were considered to be drug related.

Genitourinary System

Rare cases of hemorrhagic cystitis have been reported in patients treated with Fludarabine Phosphate for Injection.

Skin

Skin toxicity, consisting primarily of skin rashes, has been reported in patients treated with Fludarabine Phosphate for Injection. Erythema multiforme, Stevens-Johnson syndrome, toxic epidermal necrolysis and pemphigus have been reported, with fatal outcomes in some cases.

Neoplasms

Worsening or flare-up of pre-existing skin cancer lesions, as well as new onset of skin cancer, has been reported in patients during or after treatment with Fludarabine Phosphate for Injection.

Hepatobiliary Disorders

Elevations of hepatic enzyme levels have been reported.

Data in the following table are derived from the 133 patients with CLL who received Fludarabine Phosphate for Injection in the MDAH and SWOG studies.

PERCENT OF CLL PATIENTS REPORTING NONHEMATOLOGIC ADVERSE EVENTS
ADVERSE EVENTS | MDAH (N=101) | SWOG (N=32)
ANY ADVERSE EVENT | 88% | 91%
BODY AS A WHOLE | 72 | 84
FEVER | 60 | 69
CHILLS | 11 | 19
FATIGUE | 10 | 38
INFECTION | 33 | 44
PAIN | 20 | 22
MALAISE | 8 | 6
DIAPHORESIS | 1 | 13
ALOPECIA | 0 | 3
ANAPHYLAXIS | 1 | 0
HEMORRHAGE | 1 | 0
HYPERGLYCEMIA | 1 | 6
DEHYDRATION | 1 | 0
NEUROLOGICAL | 21 | 69
WEAKNESS | 9 | 65
PARESTHESIA | 4 | 12
HEADACHE | 3 | 0
VISUAL DISTURBANCE | 3 | 15
HEARING LOSS | 2 | 6
SLEEP DISORDER | 1 | 3
DEPRESSION | 1 | 0
CEREBELLAR SYNDROME | 1 | 0
IMPAIRED MENTATION | 1 | 0
PULMONARY | 35 | 69
COUGH | 10 | 44
PNEUMONIA | 16 | 22
DYSPNEA | 9 | 22
SINUSITIS | 5 | 0
PHARYNGITIS | 0 | 9
UPPER RESPIRATORY INFECTION | 2 | 16
ALLERGIC PNEUMONITIS | 0 | 6
EPISTAXIS | 1 | 0
HEMOPTYSIS | 1 | 6
BRONCHITIS | 1 | 0
HYPOXIA | 1 | 0
GASTROINTESTINAL | 46 | 63
NAUSEA/VOMITING | 36 | 31
DIARRHEA | 15 | 13
ANOREXIA | 7 | 34
STOMATITIS | 9 | 0
GI BLEEDING | 3 | 13
ESOPHAGITIS | 3 | 0
MUCOSITIS | 2 | 0
LIVER FAILURE | 1 | 0
ABNORMAL LIVER FUNCTION TEST | 1 | 3
CHOLELITHIASIS | 0 | 3
CONSTIPATION | 1 | 3
DYSPHAGIA | 1 | 0
CUTANEOUS | 17 | 18
RASH | 15 | 15
PRURITUS | 1 | 3
SEBORRHEA | 1 | 0
GENITOURINARY | 12 | 22
DYSURIA | 4 | 3
URINARY INFECTION | 2 | 15
HEMATURIA | 2 | 3
RENAL FAILURE | 1 | 0
ABNORMAL RENAL FUNCTION TEST | 1 | 0
PROTEINURIA | 1 | 0
HESITANCY | 0 | 3
CARDIOVASCULAR | 12 | 38
EDEMA | 8 | 19
ANGINA | 0 | 6
CONGESTIVE HEART FAILURE | 0 | 3
ARRHYTHMIA | 0 | 3
SUPRAVENTRICULAR TACHYCARDIA | 0 | 3
MYOCARDIAL INFARCTION | 0 | 3
DEEP VENOUS THROMBOSIS | 1 | 3
PHLEBITIS | 1 | 3
TRANSIENT ISCHEMIC ATTACK | 1 | 0
ANEURYSM | 1 | 0
CEREBROVASCULAR ACCIDENT | 0 | 3
MUSCULOSKELETAL | 7 | 16
MYALGIA | 4 | 16
OSTEOPOROSIS | 2 | 0
ARTHRALGIA | 1 | 0
TUMOR LYSIS SYNDROME | 1 | 0

More than 3000 adult patients received Fludarabine Phosphate for Injection in studies of other leukemias, lymphomas, and other solid tumors. The spectrum of adverse effects reported in these studies was consistent with the data presented above.

To report SUSPECTED ADVERSE EVENTS, contact Teva at 1-888-838-2872 or FDA at 1-800-FDA-1088 or http://www.fda.gov/medwatch for voluntary reporting of adverse reactions.

OVERDOSAGE

High doses of Fludarabine Phosphate for Injection (see WARNINGS section) have been associated with an irreversible central nervous system toxicity characterized by delayed blindness, coma and death. High doses are also associated with severe thrombocytopenia and neutropenia due to bone marrow suppression. There is no known specific antidote for Fludarabine Phosphate for Injection overdosage. Treatment consists of drug discontinuation and supportive therapy.

DOSAGE AND ADMINISTRATION

Usual Dose

The recommended adult dose of Fludarabine Phosphate for Injection is 25 mg/m^2 administered intravenously over a period of approximately 30 minutes daily for five consecutive days. Each 5 day course of treatment should commence every 28 days. Dosage may be decreased or delayed based on evidence of hematologic or nonhematologic toxicity. Physicians should consider delaying or discontinuing the drug if neurotoxicity occurs.

A number of clinical settings may predispose to increased toxicity from Fludarabine Phosphate for Injection. These include advanced age, renal impairment, and bone marrow impairment. Such patients should be monitored closely for excessive toxicity and the dose modified accordingly.

The optimal duration of treatment has not been clearly established. It is recommended that three additional cycles of Fludarabine Phosphate for Injection be administered following the achievement of a maximal response and then the drug should be discontinued.

Renal Impairment

Adjustments to the starting dose are recommended to provide appropriate drug exposure in patients with creatinine clearance 30 to 79 mL/min, as estimated by the Cockroft-Gault equations. These adjustments are based on a pharmacokinetic study in patients with renal impairment. Fludarabine Phosphate for Injection should not be administered to patients with creatinine clearance less than 30 mL/min.

Starting Dose Adjustment for Renal Impairment

Creatinine Clearance | Starting Dose
≥ 80 mL/min | 25 mg/m^2 (full dose)
50 to 79 mL/min | 20 mg/m^2
30 to 49 mL/min | 15 mg/m^2
< 30 mL/min | do not administer

Renally impaired patients should be monitored closely for excessive toxicity and the dose modified accordingly.

Preparation of Solutions

Fludarabine Phosphate for Injection should be prepared for parenteral use by aseptically adding Sterile Water for Injection, USP. When reconstituted with 2 mL of Sterile Water for Injection, the solid cake should fully dissolve in 15 seconds or less; each mL of the resulting solution will contain 25 mg of fludarabine phosphate, 25 mg of mannitol, and sodium hydroxide to adjust the pH to 7.7. The pH range for the final product is 7.2 to 8.2. In clinical studies, the product has been diluted in 100 cc or 125 cc of 5% Dextrose Injection, USP, or 0.9% Sodium Chloride, USP.

Reconstituted Fludarabine Phosphate for Injection contains no antimicrobial preservative and thus should be used within 8 hours of reconstitution. Care must be taken to assure the sterility of prepared solutions. Parenteral drug products should be inspected visually for particulate matter and discoloration prior to administration.

Fludarabine Phosphate for Injection should not be mixed with other drugs.

Handling and Disposal

Procedures for proper handling and disposal should be considered. Consideration should be given to handling and disposal according to guidelines issued for cytotoxic drugs. Several guidelines on this subject have been published.^1-4.

Caution should be exercised in the handling and preparation of Fludarabine Phosphate for Injection solution. The use of latex gloves and safety glasses is recommended to avoid exposure in case of breakage of the vial or other accidental spillage. If the solution contacts the skin or mucous membranes, wash thoroughly with soap and water; rinse eyes thoroughly with plain water. Avoid exposure by inhalation or by direct contact of the skin or mucous membranes.

HOW SUPPLIED

Fludarabine Phosphate for Injection, USP is a white, lyophilized solid cake. Each single-dose vial contains 50 mg of fludarabine phosphate USP, 50 mg of mannitol, and sodium hydroxide to adjust pH to 7.7. The pH range for the final product is 7.2 to 8.2.

Fludarabine Phosphate for Injection, USP, NDC 45963-609-55, is supplied in a clear glass single-dose vial and packaged in a carton.

Store at 20°C to 25°C (68°F to 77°F); excursions permitted between 15°C to 30°C (59°F to 86°F), in the original package.

The container closure is not made with natural rubber latex.

Sterile, Nonpyrogenic, Preservative-free

REFERENCES

1. Preventing Occupational Exposures to Antineoplastic and Other Hazardous Drugs in Health Care Settings. NIOSH Alert 2004-165.
2. OSHA Technical Manual, TED 1-0. 15A, Section VI: Chapter 2. Controlling Occupational Exposure to Hazardous Drugs. OSHA, 1999. http://www.osha.gov/dts/osta/otm/otm_vi_2.html
3. American Society of Health-System Pharmacists. ASHP guidelines on handling hazardous drugs. Am J Health-Syst Pharm. 2006: 63: 1172-1193.
4. Polvich, M., White, J.M., & Kelleher, L.O. (eds.) 2005. Chemotherapy and biotherapy guidelines and recommendations for practice (2nd ed.). Pittsburgh, PA: Oncology Nursing Society

Manufactured In Romania By:
Sindan Pharma SRL
11 Ion Mihalache Blvd
Bucharest 1, Romania 011171

Manufactured For:
Teva Pharmaceuticals
Parsippany, NJ 07054

Rev. A 9/2022

PACKAGE LABEL.PRINCIPAL DISPLAY PANEL

NDC 45963-609-55

Fludarabine Phosphate for Injection, USP

(Lyophilized)

50 mg/ vial

For Intravenous Use Only

MUST BE RECONSTITUTED

CAUTION: Cytotoxic Agent

Rx only

1 Single-Dose Vial